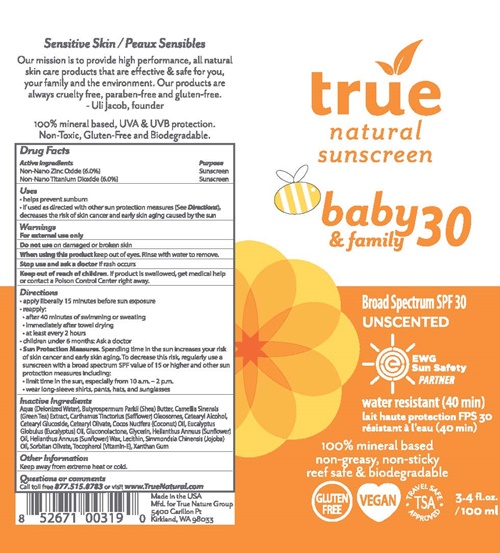 DRUG LABEL: true natural baby 30 and family
NDC: 76245-019 | Form: LOTION
Manufacturer: True Nature Group, Inc.
Category: otc | Type: HUMAN OTC DRUG LABEL
Date: 20170201

ACTIVE INGREDIENTS: ZINC OXIDE 6 g/100 mL; TITANIUM DIOXIDE 6 g/100 mL
INACTIVE INGREDIENTS: WATER; SHEA BUTTER; CAMELLIA SINENSIS FLOWER; SAFFLOWER OIL; CETOSTEARYL ALCOHOL; CETEARYL GLUCOSIDE; CETEARYL OLIVATE; COCONUT OIL; EUCALYPTUS OIL; GLUCONOLACTONE; SUNFLOWER OIL; HELIANTHUS ANNUUS SEED WAX; LECITHIN, SUNFLOWER; JOJOBA OIL; SORBITAN OLIVATE; .ALPHA.-TOCOPHEROL; XANTHAN GUM

True Natural Baby - 019

Drug Facts Active Ingredients

Non- Nano Zinc Oxide (6%)

Non-Nano Titanium Dioxide (6%)

Purpose

Sunscreen

Uses

- helps prevent sunburn
- if used as directed with other sun protection measures (See Directions), decreases the risk of skin cancer and early skin aging caused by the sun

Warnings

For external use only

Do not use

on damaged or broken skin

When using this product

keep out of eyes. Rinse with water to remove.

Stop use and ask a doctor

if rash occurs

Keep out of reach of children.

If product is swallowed, get medical help or contact a Poison Control Center right away.

Directions

- apply liberally 15 minutes before sun exposure
- reapply
- after 40 minutes of swimming or sweating
- immediately after towel drying
- at least every 2 hours
- children under 6 months: Ask a doctor
- Sun Protection Measures Spending time in the sun increases your risk of skin cancer and early skin aging. To decrease this risk, regularly use a sunscreen with a broad with a broad spectrum SPF value of 15 or higher and other sun protection measures including:
  - limit time in the sun, especially from 10 a.m. - 2 p.m.
  - wear long-sleeved shirts, pants, hats, and sunglasses

Inactive Ingredients

Aqua (Delonized Water), Butyrospermum Parkii (Shea) Butter, Camellia Sinensis (Green Tea) Extract, Carthamus Tinctorius (Safflower) Oleosomes, Cetearyl Alcohol, Cetearyl Glucoside, Cetearyl Olivate, Cocos Nucifera (Coconut Oil), Eucalptus Globulus (Eucalptus) Oil, Gluconolctone, Glycerin, Helianthus Annuus (Sunflower)Oil, Helianthus Annuus (Sunflower) Wax, Lecithin, Simmondsia Chinensis (Jojoba) Oil, Sorbitan Olivate, Tocopherol (Vitamin-E), Xanthan Gum

Other Information

Keep away from extreme heat or cold.

Questions or comments

Call toll free 877.515.8783 or visit www.True.Natural.com

true natural baby 30 product label

true

natural
sunscreen

baby 30
& family

Broad Spectrum SPF 30 UNSCENTED

EWG Sun Safety Partner

water resistant (40 min)

lait haute protection FPS 50

100% mineralbased
non-greasy, non-sticky
reef safe & biodegradable

GLUTEN FREE VEGAN TSA -TRAVEL SAFE APPROVED

3-4 fl oz./ 100 ml

Made in the USA

Mfd for True Nature Group
5400 Carillon Pt
Kirkland, WA 98033

Sensative Skin

Our mission is to provide high performance, all natural skin care products that are effective & safe for you, your family and the environment. Our products are always cruelty free, paraben-free, and gluten-free.

UI Jacob, founder

100% mineral based, UVA & UVB protection
Non-Toxic, Gluten-Free and Biodegradable.